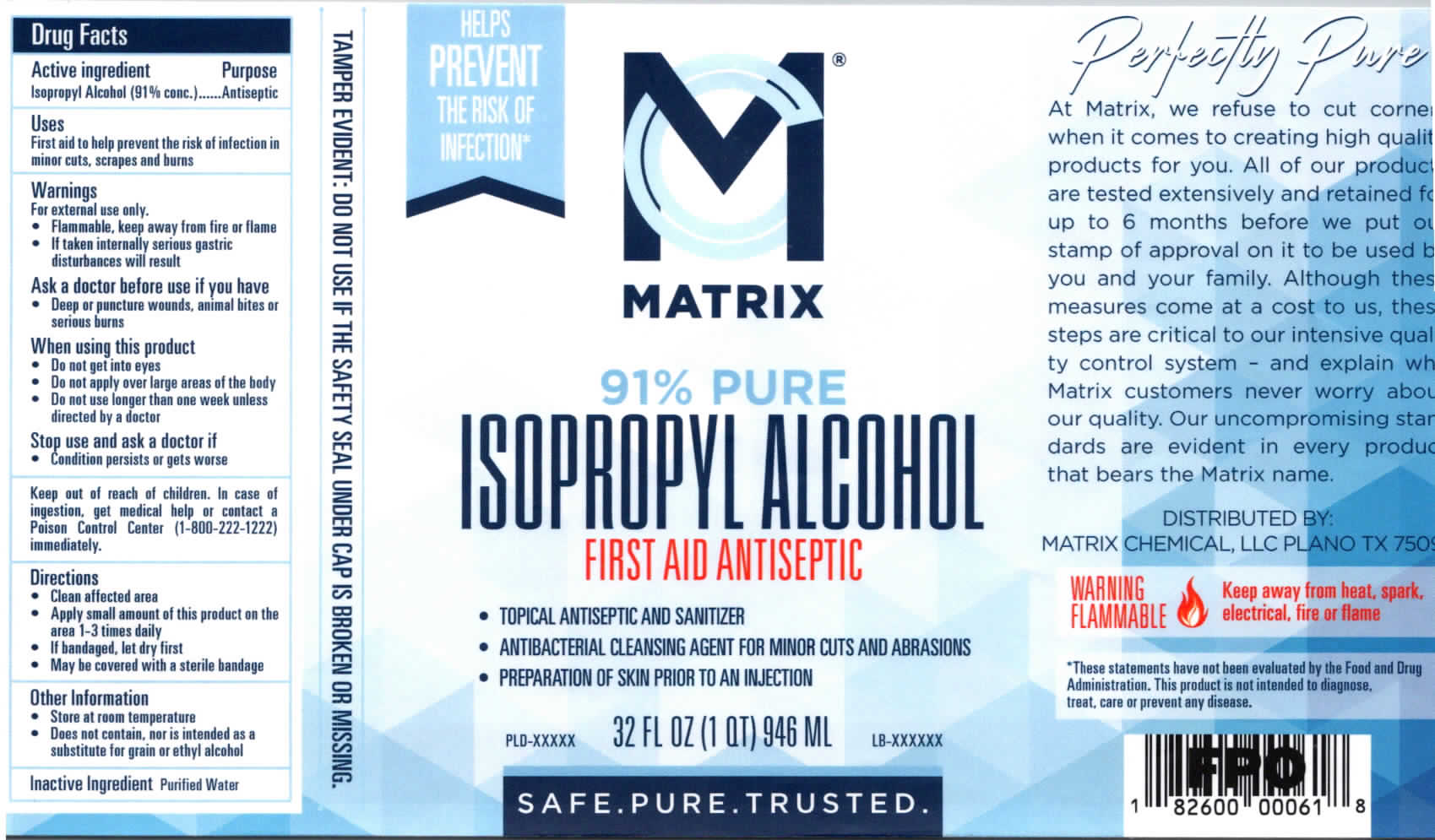 DRUG LABEL: 91 Percent Pure Isopropyl Alcohol
NDC: 77285-277 | Form: LIQUID
Manufacturer: MATRIX CHEMICAL LLC
Category: otc | Type: HUMAN OTC DRUG LABEL
Date: 20201120

ACTIVE INGREDIENTS: ISOPROPYL ALCOHOL 91 mL/100 mL
INACTIVE INGREDIENTS: WATER 9 mL/100 mL

Isopropyl Alcohol 91 Percent

Drug Facts

Active Ingredient

Isopropyl Alcohol (91% conc.)

Purpose

First aid antiseptic

Uses

First aid to help prevent the risk of infection in minor cuts, scrapes and burns

Warnings

For external use only.

- Flammable, keep away from fire or flame
- If taken internaly serious gastric disturbancves will result

Ask a doctor before use if you have

- Deep or puncture wounds, animal bites or serious burns

When using this product

- Do not get into eyes
- Do not apply over large areas of the body
- Do not use longer than one week unless directed by a doctor

Stop use and ask a doctor if

- Condition persists or gets worse

Keep out of reach of children.

In case of ingestion, get medical help or contact a Poison Control Center (1-800-222-1222) immediately.

Directions

- Clean affected area
- Apply small amount of this product on the area 1-3 times daily
- If bandaged, let dry first
- May be covered with a sterile bandage

Other Information

- Store at room temperature
- Does not contain, nor is intended as a substitute for grain or ethyl alcohol

Inactive Ingredient

Purified Water

Package Label

MATRIX

91% PURE

ISOPROPYL ALCOHOL

FIRST AID ANTISEPTIC

32 FL OZ (1 QT) 946 ML

Isopropyl Alcohol 91 - 32oz.jpg